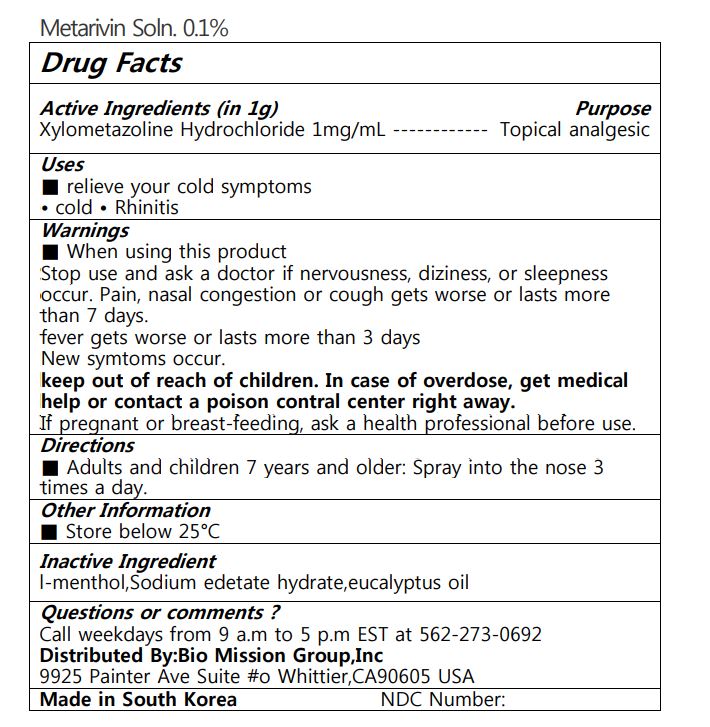 DRUG LABEL: Metarivin Soln. 0.1%
NDC: 72988-0030 | Form: LIQUID
Manufacturer: Lydia Co., Ltd.
Category: otc | Type: HUMAN OTC DRUG LABEL
Date: 20220930

ACTIVE INGREDIENTS: XYLOMETAZOLINE HYDROCHLORIDE 1 mg/1 mL
INACTIVE INGREDIENTS: COBALT DISODIUM EDETATE; EUCALYPTUS OIL; LEVOMENTHOL

ACTIVE INGREDIENT

Xylometazoline Hydrochloride

PURPOSE

■ relieve your cold symptoms cold Rhinitis

Keep out of reach of children

INDICATIONS AND USAGE

Adults and children 7 years and older: Spray into the nose 3 times a day

■ When using this product Stop use and ask a doctor if nervousness, diziness, or sleepness occur. Pain, nasal congestion or cough gets worse or lasts more than 7 days. fever gets worse or lasts more than 3 days New symtoms occur. keep out of reach of children. In case of overdose, get medical help or contact a poison contral center right away. If pregnant or breast-feeding, ask a health professional before use.

INACTIVE INGREDIENT

l-menthol, eucalyptus oil, etc

DOSAGE AND ADMINISTRATION

for nasal use